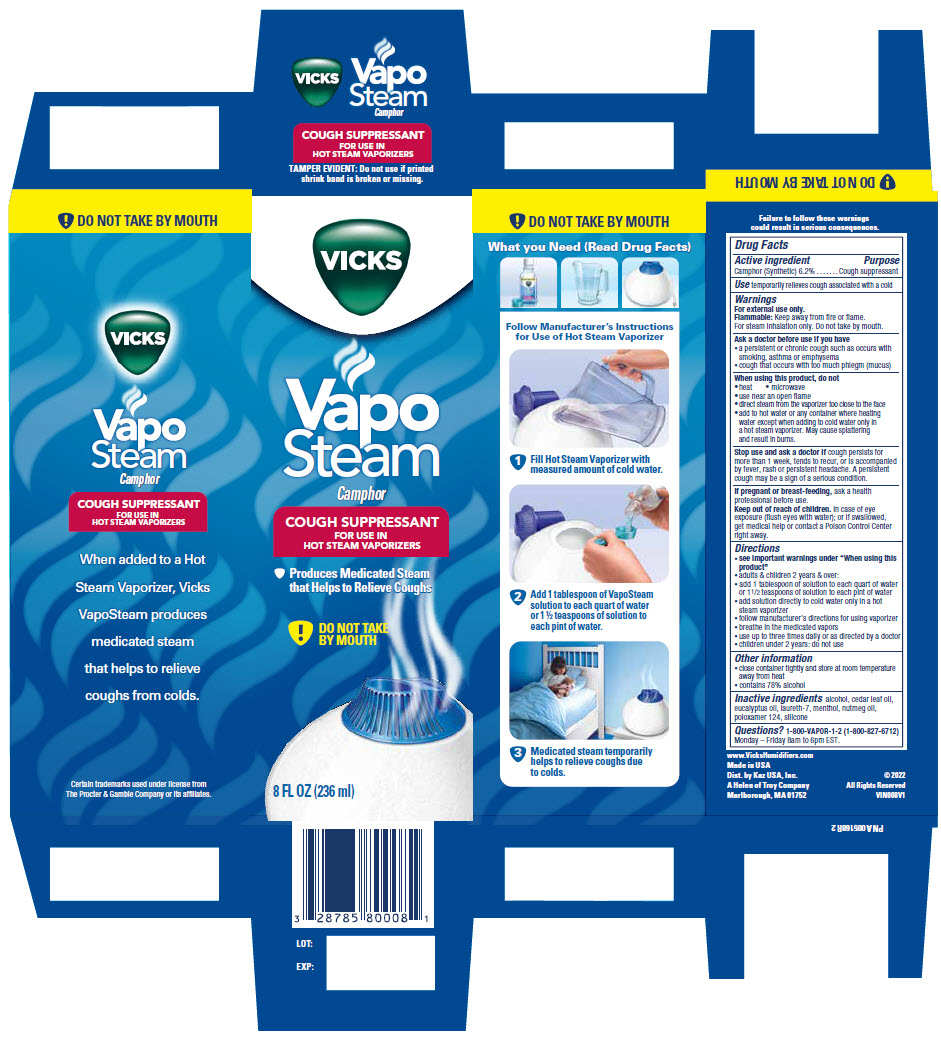 DRUG LABEL: Vicks VapoSteam
NDC: 69901-522 | Form: LIQUID
Manufacturer: Kaz USA, Inc
Category: otc | Type: HUMAN OTC DRUG LABEL
Date: 20250110

ACTIVE INGREDIENTS: Camphor (synthetic) 0.062 g/1 mL
INACTIVE INGREDIENTS: Alcohol; Menthol, Unspecified Form; Poloxamer 124; Laureth-7; Eucalyptus Oil; Cedar Leaf Oil; Nutmeg Oil

Vicks® VapoSteam®

Drug Facts

Active ingredient

Camphor (Synthetic) 6.2%

Purpose

Cough suppressant

Use

temporarily relieves cough associated with a cold

Warnings

For external use only.

Flammable: Keep away from fire or flame. For steam inhalation only. Do not take by mouth.

Ask a doctor before use if you have

- a persistent or chronic cough such as occurs with smoking, asthma or emphysema
- cough that occurs with too much phlegm (mucus)

When using this product, do not

- heat
- microwave
- use near an open flame
- direct steam from the vaporizer too close to the face
- add to hot water or any container where heating water except when adding to cold water only in a hot steam vaporizer. May cause splattering and result in burns.

Stop use and ask a doctor if cough persists for more than 1 week, tends to recur, or is accompanied by fever, rash or persistent headache. A persistent cough may be a sign of a serious condition.

PREGNANCY OR BREAST FEEDING

If pregnant or breast-feeding, ask a health professional before use.

Keep out of reach of children. In case of eye exposure (flush eyes with water); or if swallowed, seek medical help or contact a Poison Control Center right away.

Directions

- see important warnings under "When using this product"
- adults & children 2 years & over:
  - add 1 tablespoon of solution to each quart of water or 1½ teaspoons of solution to each pint of water
  - add solution directly to cold water only in a hot steam vaporizer
  - follow manufacturer's directions for using vaporizer
  - breathe in the medicated vapors
  - use up to three times daily or as directed by a doctor
- children under 2 years: do not use

Other information

- close container tightly and store at room temperature away from heat
- contains 78% alcohol

Inactive ingredients

alcohol, cedarleaf oil, eucalyptus oil, laureth-7, menthol, nutmeg oil, poloxamer 124, silicone

Questions?

1-800-VAPOR-1-2 (1-800-827-6712)

Dist. by Kaz USA, Inc.,
A Helen of Troy Company,
Marlborough, MA 01752

PRINCIPAL DISPLAY PANEL - 236 ml Bottle Carton

VICKS

Vapo
Steam

Camphor

COUGH SUPPRESSANT
FOR USE IN
HOT STEAM VAPORIZERS

- Produces Medicated Steam
  that Helps to Relieve Coughs

!
DO NOT TAKE
BY MOUTH

8 FL OZ (236 ml)